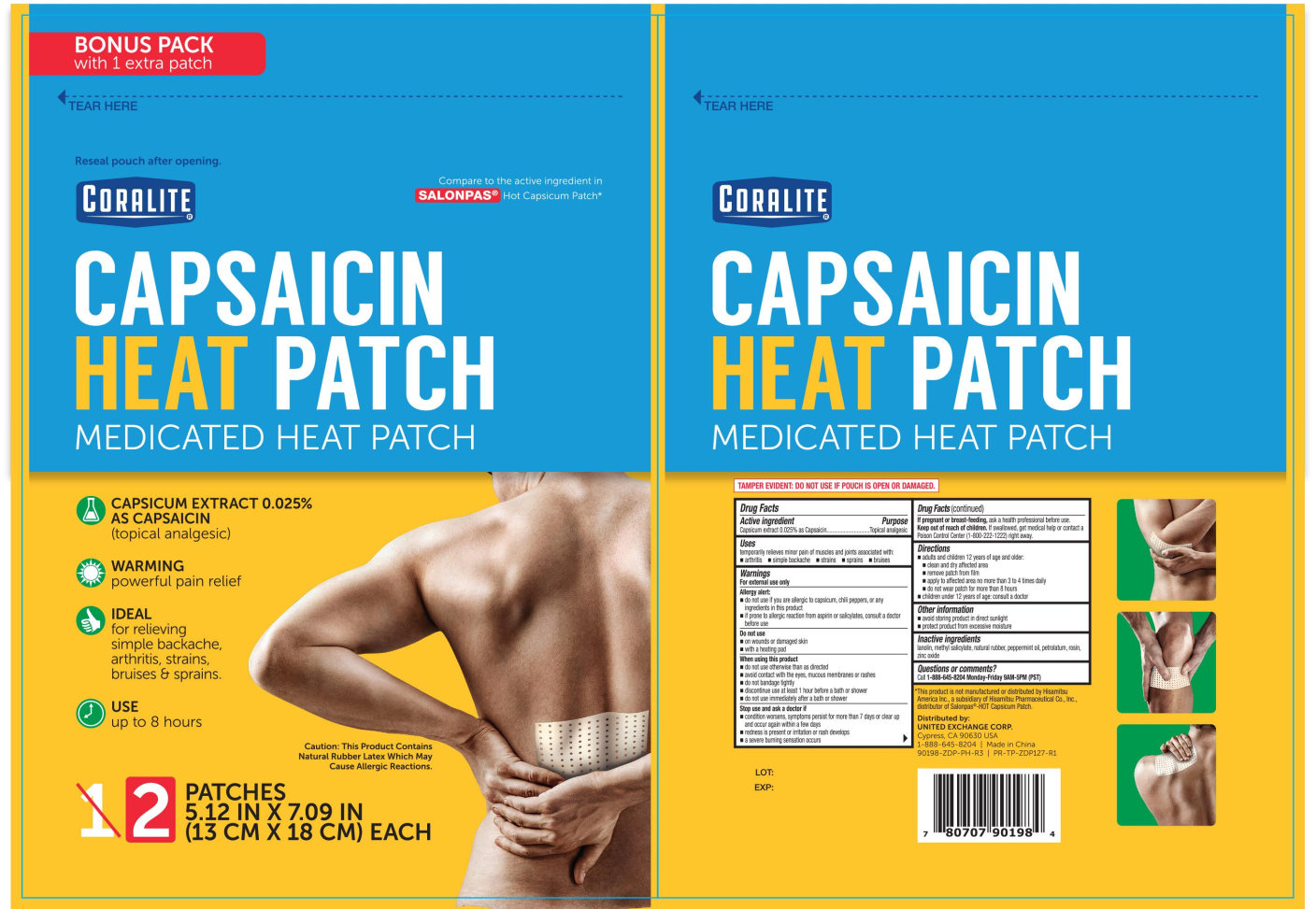 DRUG LABEL: Coralite Medicated Heat
NDC: 65923-123 | Form: PATCH
Manufacturer: United Exchange Corp.
Category: otc | Type: HUMAN OTC DRUG LABEL
Date: 20251031

ACTIVE INGREDIENTS: CAPSAICIN 249 mg/1 1
INACTIVE INGREDIENTS: ZINC OXIDE; STYRENE/ISOPRENE/STYRENE BLOCK COPOLYMER; TITANIUM DIOXIDE; LANOLIN; BUTYLATED HYDROXYTOLUENE; DIPHENHYDRAMINE HYDROCHLORIDE; GLYCERYL ROSINATE; NATURAL LATEX RUBBER; PETROLATUM; POLYISOBUTYLENE (85000 MW)

Coralite Hot Capsaicin Patch 1ct, 2ct (NB SalonPas) 90132A and 90198

Active ingredient Purpose

Capsicum Extract Capsaicin 0.025%..............................Topical Analgesic

Uses

For temporary relief of minor aches and pains of muscles & joints associated with:

- Simple Backache
- Arthritis
- Strains
- Bruises
- Sprains

Warnings

For external use only

Allergy alert:

- do not use if you are allergic to capsicum, chili peppers, or any ingredients in this product
- if prone to allergic reaction from aspirin or salicylates, consult a doctor before use

Do not use:

- on wounds or damaged skin.
- with a heating pad.

When using this product:

- do not use otherwise than directed
- avoid contact with the eyes, mucous membranes or rashes
- do not bandage tightly
- discontinue use at least 1 hour before a bath or shower
- do not use immediately after a bath or shower

stop use and ask a doctor if:

- condition worsens, symptoms persist for more than 7 days or clear up and occur again within a few days
- redness is present or irritation or rash develops
- a severe burning sensation occurs

Keep out of reach of children.

If swallowed, get medical help or contact a Poison Control Center (1-800-222-1222) right away.

PREGNANCY OR BREAST FEEDING

If pregnant or breastfeeding, ask a health professional before use.

Directions

- adults and children 12 years of age and older:
- clean and dry affected area
- remove patch from film
- apply to affected area no more than 3 to 4 times daily
- do not wear patch more than 8 hours
- children under 12 years of age: consult a doctor

Other information

- Avoid storing product in direct sunlight.
- Protect product from excessive moisture.

Inactive ingredients

butylated hydroxytoluene, diphenhydramine, hydrochloride, glyceryl, rosinate, lanolin, natural rubber, petrolatum, polyisobutylene (85,000 MW), styrene-isoprene-styrene block copolymer, titanium dioxide, zinc oxide

DOSAGE AND ADMINISTRATION

Distributed by:

United Exchange Corp.

5836 Corporate Ave.

Cypress, CA 90630 USA

Made in China